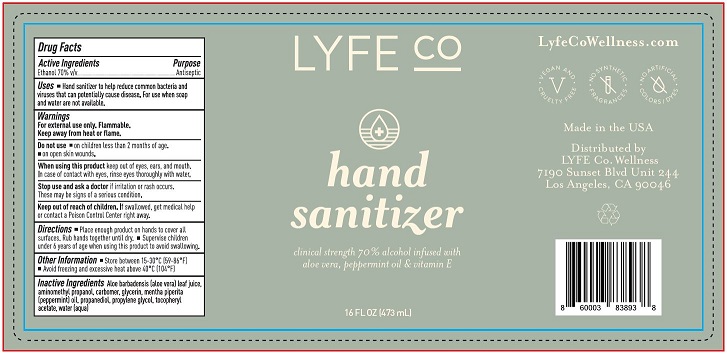 DRUG LABEL: LYFE CO HAND SANITIZER
NDC: 78559-101 | Form: GEL
Manufacturer: LYFE CO WELLNESS LLC
Category: otc | Type: HUMAN OTC DRUG LABEL
Date: 20200604

ACTIVE INGREDIENTS: ALCOHOL 70 mL/100 mL
INACTIVE INGREDIENTS: ALOE VERA LEAF; AMINOMETHYL PROPANEDIOL; CARBOMER HOMOPOLYMER, UNSPECIFIED TYPE; GLYCERIN; PEPPERMINT OIL; PROPANEDIOL; PROPYLENE GLYCOL; .ALPHA.-TOCOPHEROL ACETATE; WATER

LYFE CO HAND SANITIZER (70% ETHANOL)

ACTIVE INGREDIENT

ETHANOL 70%

PURPOSE

ANTISEPTIC

USES

HAND SANITIZER TO HELP REDUCE COMMON BACTERIA AND VIRUSES THAT CAN POTENTIALLY CAUSE DISEASE. FOR USE WHEN SOAP AND WATER ARE NOT AVAILABLE.

WARNINGS

FOR EXTERNAL USE ONLY. FLAMMABLE.

KEEP AWAY FROM HEAT OR FLAME.

DO NOT USE

- ON CHILDREN LESS THAN 2 MONTHS OF AGE.
- ON OPEN SKIN WOUNDS.

WHEN USING THIS PRODUCT KEEP OUT OF EYES, EARS, AND MOUTH. IN CASE OF CONTACT WITH EYES, RINSE EYES THOROUGHLY WITH WATER.

STOP USE AND ASK A DOCTOR IF IRRITATION OR RASH OCCURS. THESE MAY BE SIGNS OF A SERIOUS CONDITION.

KEEP OUT OF REACH OF CHILDREN. IF SWALLOWED, GET MEDICAL HELP OR CONTACT A POISON CONTROL CENTER RIGHT AWAY.

DIRECTIONS

- PLACE ENOUGH PRODUCT ON HANDS TO COVER ALL SURFACES. RUB HANDS TOGETHER UNTIL DRY.
- SUPERVISE CHILDREN UNDER 6 YEARS OF AGE WHEN USING THIS PRODUCT TO AVOID SWALLOWING.

OTHER INFORMATION

- STORE BETWEEN 15-30°C (59-86°F)
- AVOID FREEZING AND EXCESSIVE HEAT ABOVE 40°C (104°F)

INACTIVE INGREDIENTS

ALOE BARBADENSIS (ALOE VERA) LEAF JUICE, AMINOMETHYL PROPANOL, CARBOMER, GLYCERIN, MENTHA PIPERITA (PEPPERMINT) OIL, PROPANEDIOL, PROPYLENE GLYCOL, TOCOPHERYL ACETATE, WATER (AQUA)